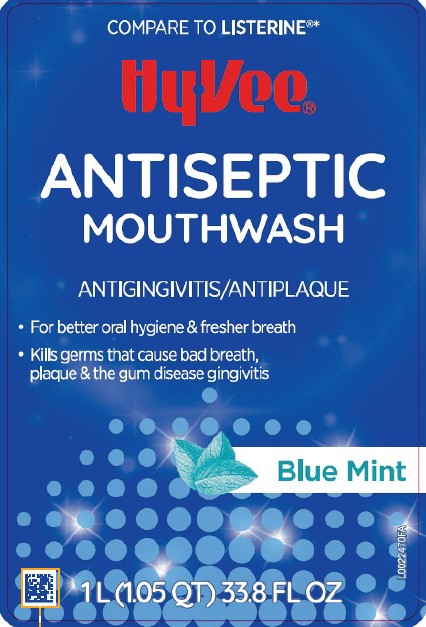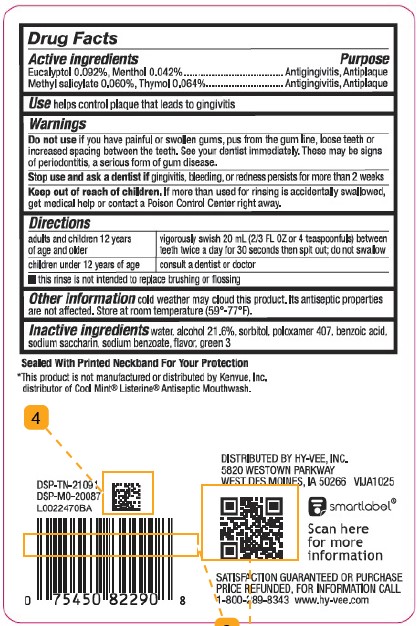 DRUG LABEL: Antispetic
NDC: 42507-963 | Form: MOUTHWASH
Manufacturer: Hy-Vee, Inc.
Category: otc | Type: HUMAN OTC DRUG LABEL
Date: 20260204

ACTIVE INGREDIENTS: THYMOL 0.64 mg/1 mL; METHYL SALICYLATE 0.6 mg/1 mL; MENTHOL 0.42 mg/1 mL; EUCALYPTOL 0.92 mg/1 mL
INACTIVE INGREDIENTS: SACCHARIN SODIUM; ALCOHOL; BENZOIC ACID; SORBITOL; SODIUM BENZOATE; WATER; FD&C GREEN NO. 3; POLOXAMER 407

Hy-Vee 664.003/664AT Rev2-AU
Blue Mint Antiseptic Mouthrinse

Active ingredients

Eucalyptol 0.092%

Menthol 0.042%

Methyl salicylate 0.060%

Thymol 0.064%

Purpose

Antigingivitis, Antiplaque

Use

helps control plaque that leads to gingivitis

Warnings

for this product

Do not use

if you have painful or swollen gums, pus from the gum line, loose teeth or increased spacing between the teeth. See your dentist immediately. These may be signs of periodontitis, a serious form of gum disease.

Stop use and ask a dentist if

gingivitis, bleeding, or redness persists for more than 2 weeks.

Keep out of reach of children.

If more than used for rinsing is accidentally swallowed, get medical help or contact a Poison Control Center right away.

Directions

adults and children 12 years of age and older - vigorously swish 20 mL (2/3 FL OZ or 4 teaspoonfuls) between teeth twice a day for 30 seconds then spit out; do not swallow

children under 12 years of age - consult a dentist or doctor

- this rinse is not intended to replace brushing or flossing

Other information

cold weather may cloud this product. Its antiseptic properties are not affected. Store at room temperature (59°-77°F).

Inactive ingredients

water, alcohol 21.6%, sorbitol, poloxamer 407, benzoic acid, sodium saccharin, sodium benzoate, flavor, green 3

Tamper Evident Statement

Sealed With Printed Neckband For Your Protection

Disclaimer

*This product is not manufactured or distributed by Kenvue, Inc., distributor of CoolMint® Listerine® Antiseptic Mouthwash.

Adverse Reaction

DISTRIBUTED BY HY-VEE, INC.

5820 WESTOWN PARKWAY

WEST DES MOINES, IA 50266

DSP-TN-21091

DSP-MO-20087

smartlabel

Scan here for more information

SATISFACTION GUARANTEED OR PURCHASE PRICE REFUNDED, FOR INFORMATION CALL 1-800-289-8343 www.hy-vee.com

Principal Display Panel

COMPARE TO LISTERINE®*

Hy-Vee®

ANTISEPTIC MOUTHWASH

ANTIGINGIVITIS/ANTIPLAQUE

- For better oral hygiene & fresher breath
- Kills germs that cause bad breath, plaque & the gum disease gingivits

Blue Mint

1 L (1.05 QT) 33.8 FL OZ